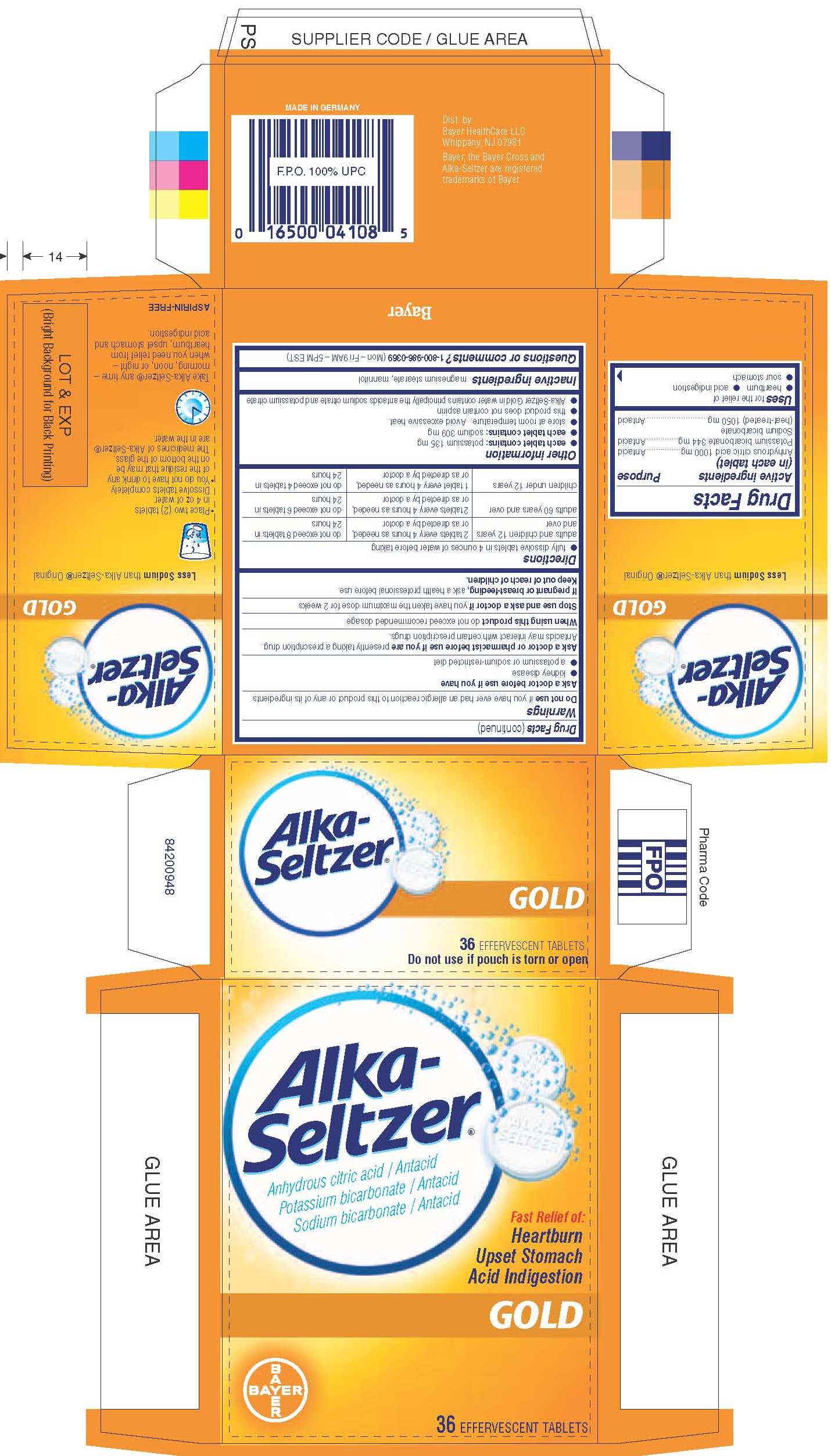 DRUG LABEL: Alka-Seltzer Gold
NDC: 0280-4100 | Form: TABLET, EFFERVESCENT
Manufacturer: Bayer HealthCare LLC.
Category: otc | Type: HUMAN OTC DRUG LABEL
Date: 20251204

ACTIVE INGREDIENTS: CITRIC ACID MONOHYDRATE 1000 mg/1 1; POTASSIUM BICARBONATE 344 mg/1 1; SODIUM BICARBONATE 1050 mg/1 1
INACTIVE INGREDIENTS: MAGNESIUM STEARATE; MANNITOL

Alka-Seltzer Gold

Drug Facts

Active Ingredients

Anhydrous citric acid 1000 mg.................................………Antacid

Potassium bicarbonate 344 mg.…..………………….……..Antacid

Sodium bicarbonate (heat-treated) 1050 mg………………Antacid

Purpose

Antacid

INDICATIONS AND USAGE

Uses for the relief of

● heartburn ● acid indigestion ● sour stomach

Do not use if you have ever had an allergic reaction to this product or any of its ingredients

Ask a doctor before use if you have

- kidney disease
- a potassium or sodium-restricted diet

Ask a doctor or pharmacist before use if you are presently taking a prescription drug. Antacids may interact with certain prescription drugs.

When using this product do not exceed recommended dosage

Stop use and ask a doctor if you have taken the maximum dose for 2 weeks

PREGNANCY OR BREAST FEEDING

If pregnant or breast-feeding, ask a health professional before use.

Keep out of reach of children

Directions

● fully dissolve tablets in 4 ounces of water before taking

adults and children 12 years and over | 2 tablets every 4 hours as needed, or asdirected by a doctor | do not exceed8 tablets in 24 hours
adults 60 years and over | 2 tablets every 4 hours as needed, or as directed by a doctor | do not exceed 6 tablets in 24 hours
children under 12 years | 1 tablet every 4 hours as needed, or as directed by a doctor | do not exceed 4 tablets in 24 hours

Other information

● each tablet contains: potassium 135 mg

● each tablet contains: sodium 309 mg

● store at room temperature. Avoid excessive heat.

● this product does not contain aspirin

● Alka-Seltzer Gold in water contains principally the

antacids sodium citrate and potassium citrate

Inactive ingredients

Inactive ingredients magnesium stearate, mannitol

Questions or comments?1-800-986-0369 (Mon – Fri 9AM – 5PM EST)

WARNINGS

Reye’s syndrome: Children and teenagers who have or are recovering from chicken pox or flu-like symptoms should not use this product. When using this product, if changes in behavior with nausea and vomiting occur, consult a doctor because these symptoms could be an early sign of Reye’s syndrome, a rare but serious illness.

Allergy alert: Aspirin may cause a severe allergic reaction which may include:

· hives · facial swelling · asthma (wheezing) · shock

Stomach bleeding warning: This product contains an NSAID, which may cause severe stomach bleeding. The chance is

higher if you

● are age 60 or older

● have had stomach ulcers or bleeding problems

● take a blood thinning (anticoagulant) or steroid drug

● take other drugs containing prescription or nonprescription

NSAIDs (aspirin, ibuprofen, naproxen, or others)

● have 3 or more alcoholic drinks every day while using this

product

● take more or for a longer time than directed